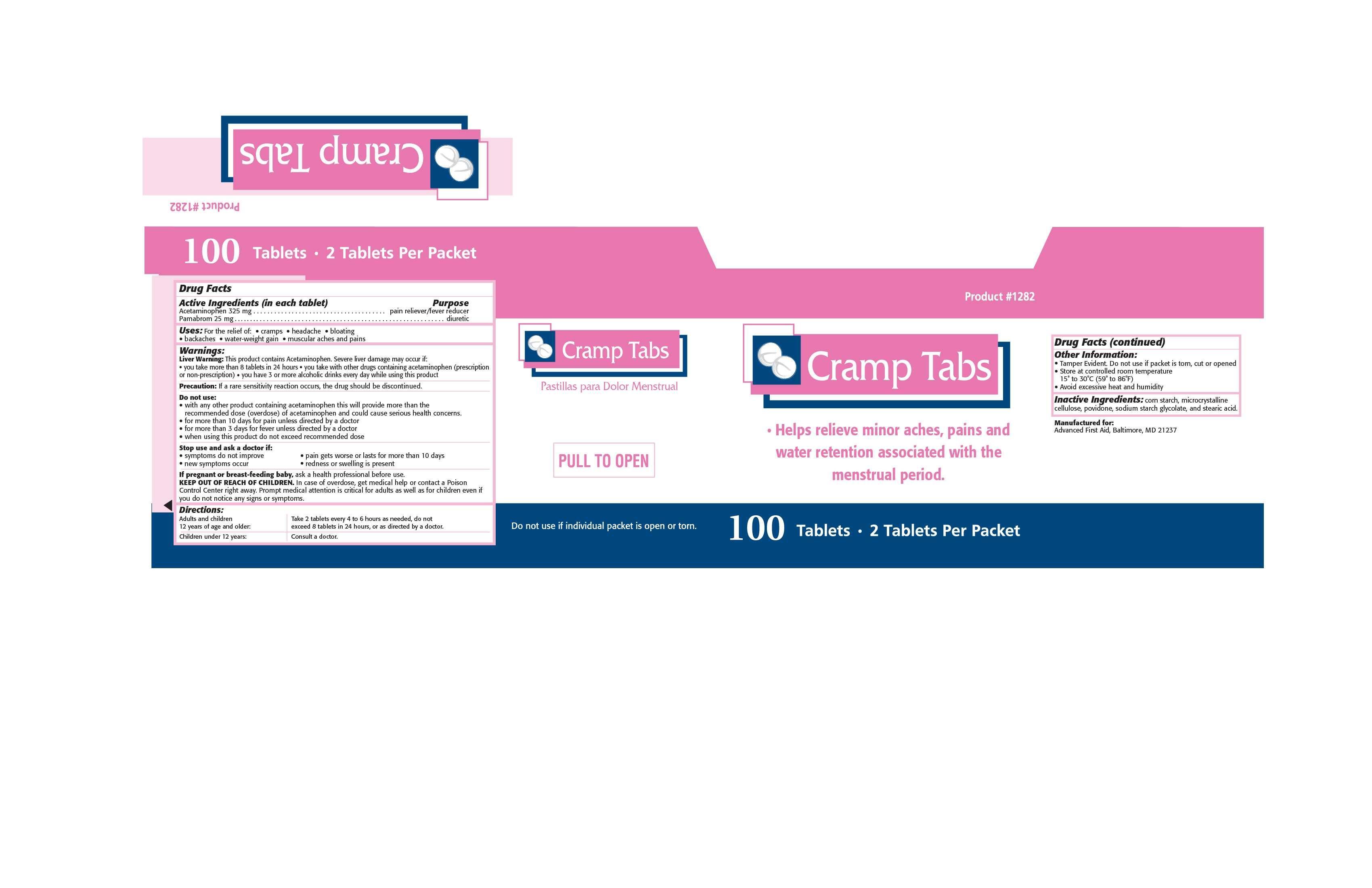 DRUG LABEL: Cramp Tabs
NDC: 67060-700 | Form: TABLET
Manufacturer: ADVANCED FIRST AID, INC.
Category: otc | Type: HUMAN OTC DRUG LABEL
Date: 20150810

ACTIVE INGREDIENTS: ACETAMINOPHEN 325 1/1 1; pamabrom 25 1/1 1
INACTIVE INGREDIENTS: CELLULOSE, MICROCRYSTALLINE; POVIDONE K30; STARCH, CORN; STEARIC ACID; sodium starch glycolate type a corn

ACTIVE INGREDIENT IN EACH TABLET- ACETAMINOPHEN 250 MG, pamabrom 25 MG

PURPOSE

PAIN RELIEVER/FEVER REDUCER WITH Diuretic

INDICATIONS AND USAGE

Uses: For the relief of:

- cramps
- headache
- bloating
- backaches
- water-weight gain
- muscular aches and pains

Warnings:

Liver Warning:

This product contains Acetaminophen. Severe liver damage may occur if:

•you take more than 8 tablets in 24 hours • you take with other drugs containing acetaminophen (prescription

or non-prescription)

• you have 3 or more alcoholic drinks every day while using this product

Precaution: If a rare sensitivity reaction occurs, the drug should be discontinued.

Do not use:

• with any other product containing acetaminophen this will provide more than the recommended dose (overdose) of acetaminophen and could cause serious health concerns.

• for more than 10 days for pain unless directed by a doctor

- than 3 days unless directed by a doctor
- when using this product do not exceed recommended dose

Stop use and ask a doctor if:

- symptoms do not improve
- new symptoms occur
- pain gets worse or lasts for more than 10 days
- redness or swelling is present

PREGNANCY OR BREAST FEEDING

If pregnant or breast-feeding baby,ask a health professional before use.

KEEP OUT OF REACH OF CHILDREN. In case of overdose, get medical help or

contact a Poison Control Center right away. Prompt medical attention is critical for

adults as well as for children even if you do not notice any signs or symptoms.

DOSAGE AND ADMINISTRATION

Adults and children 12 years of age and older:Take 2 tablets every 4-6 hours as

needed. Do not exceed 8 tablets in any 24 hour period, or as directed by a doctor.

Children under 12 years: Consult a doctor.

INACTIVE INGREDIENT

Inactive Ingredients: corn starch, microcrystalline cellulose, povidone, sodium starch glycolate, and stearic acid.